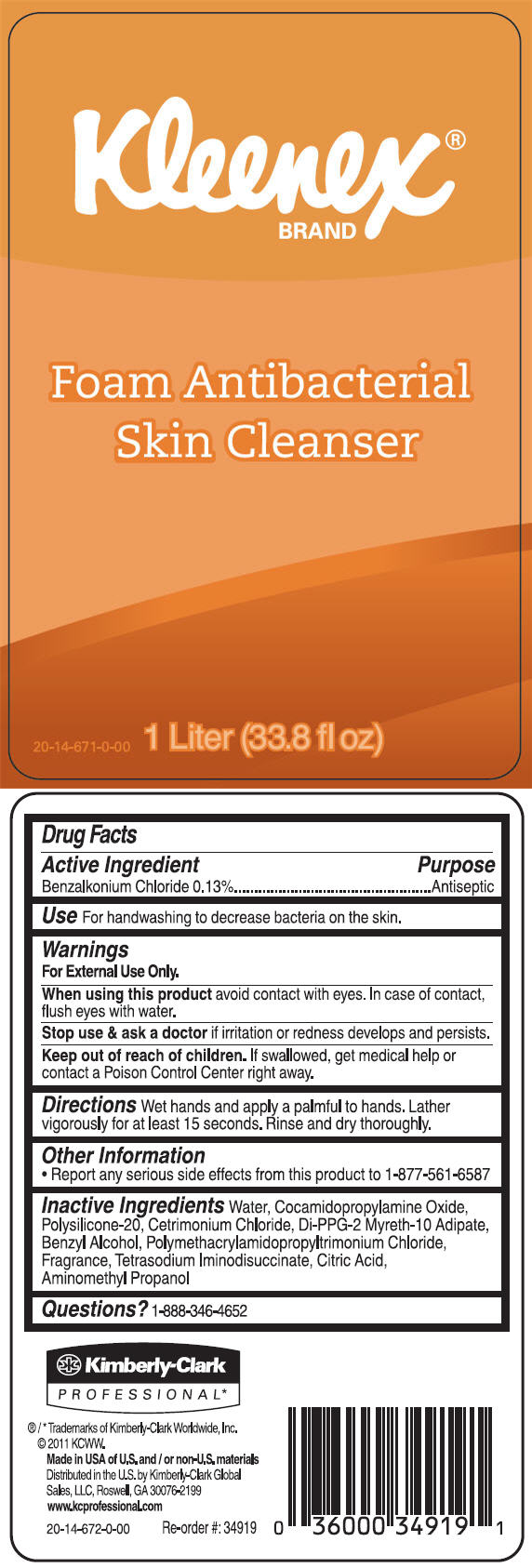 DRUG LABEL: Kleenex Antibacterial Skin Cleanser
NDC: 55118-560 | Form: SOLUTION
Manufacturer: Kimberly-Clark Corporation
Category: otc | Type: HUMAN OTC DRUG LABEL
Date: 20141112

ACTIVE INGREDIENTS: Benzalkonium Chloride 1.3 g/1 L
INACTIVE INGREDIENTS: Water; Cocamidopropylamine Oxide; Cetrimonium Chloride; Benzyl Alcohol; Citric Acid Monohydrate; Aminomethylpropanol

Kleenex® Foam Antibacterial Skin Cleanser

Drug Facts

Active Ingredient

Benzalkonium Chloride 0.13%

Purpose

Antiseptic

Use

For handwashing to decrease bacteria on the skin.

Warnings

For External Use Only.

When using this product avoid contact with eyes. In case of contact, flush eyes with water.

Stop use & ask a doctor if irritation or redness develops and persists.

Keep out of reach of children. If swallowed, get medical help or contact a Poison Control Center right away.

Directions

Wet hands and apply a palmful to hands. Lather vigorously for at least 15 seconds. Rinse and dry thoroughly.

Other Information

- Report any serious side effects from this product to 1-877-561-6587

Inactive Ingredients

Water, Cocamidopropylamine Oxide, Polysilicone-20, Cetrimonium Chloride, Di-PPG-2 Myreth-10 Adipate, Benzyl Alcohol, Polymethacrylamidopropyltrimonium Chloride, Fragrance, Tetrasodium Iminodisuccinate, Citric Acid, Aminomethyl Propanol

Questions?

1-888-346-4652

Distributed in the U.S. by Kimberly-Clark Global
Sales, LLC, Roswell, GA 30076-2199

PRINCIPAL DISPLAY PANEL - 1 Liter Carton

Kleenex®
BRAND

Foam Antibacterial
Skin Cleanser

20-14-671-0-00

1 Liter (33.8 fl oz)